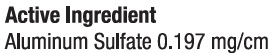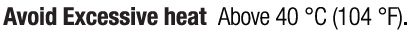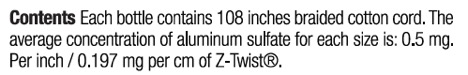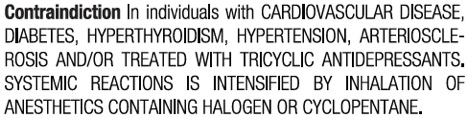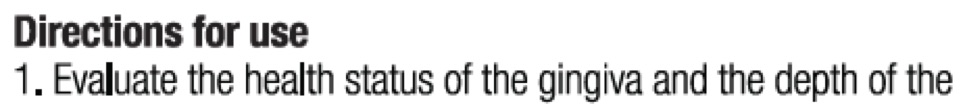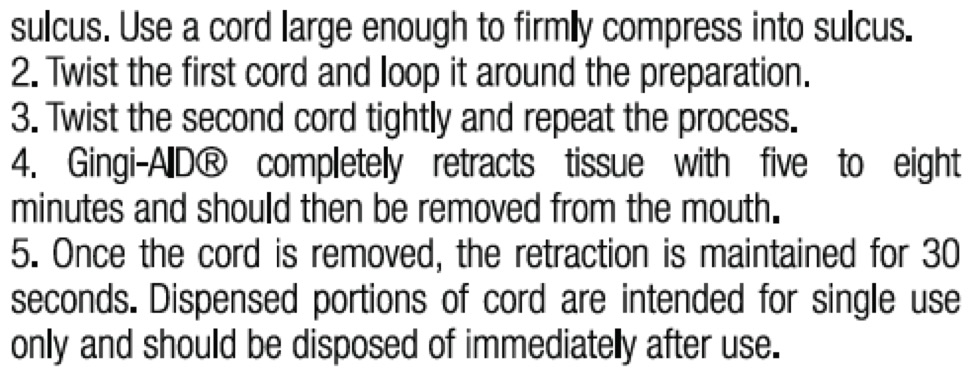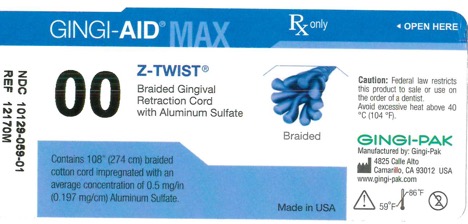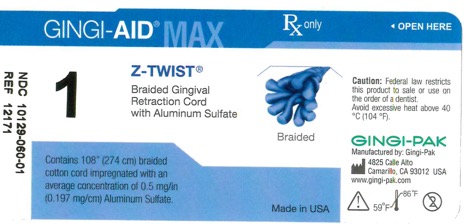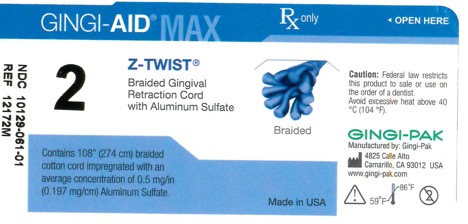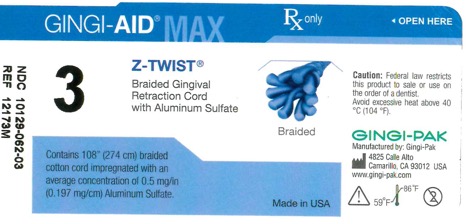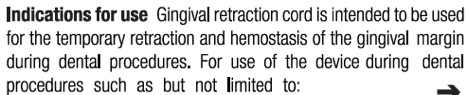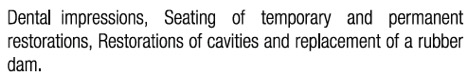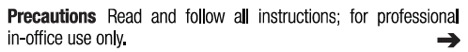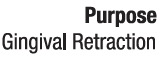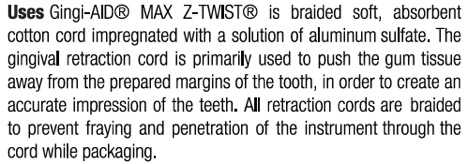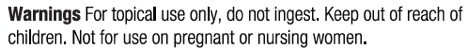 DRUG LABEL: Gingi-Aid MAX Z-Twist 1
NDC: 10129-060 | Form: SOLUTION
Manufacturer: Gingi-Pak a Division of the Belport
Category: otc | Type: HUMAN OTC DRUG LABEL
Date: 20180124

ACTIVE INGREDIENTS: ALUMINUM SULFATE 54 mg/1 1
INACTIVE INGREDIENTS: COTTON FIBER 2740 mm/1 1

Gingi-Aid MAX Z-Twist